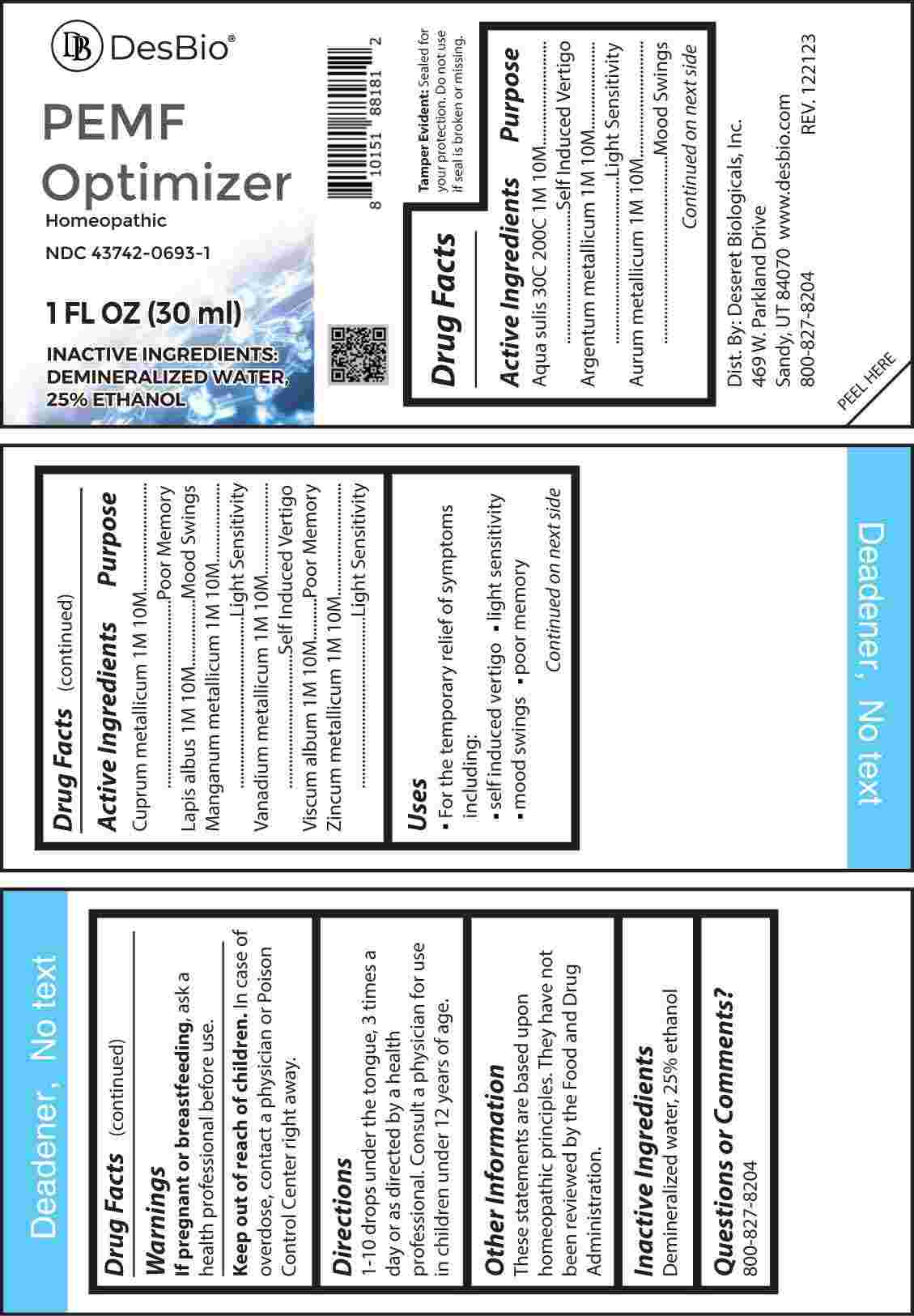 DRUG LABEL: PEMF Optimizer
NDC: 43742-0693 | Form: LIQUID
Manufacturer: Deseret Biologicals, Inc.
Category: homeopathic | Type: HUMAN OTC DRUG LABEL
Date: 20240423

ACTIVE INGREDIENTS: WATER 30 [hp_C]/1 mL; SILVER 1 [hp_M]/1 mL; GOLD 1 [hp_M]/1 mL; COPPER 1 [hp_M]/1 mL; CALCIUM HEXAFLUOROSILICATE 1 [hp_M]/1 mL; MANGANESE 1 [hp_M]/1 mL; VANADIUM 1 [hp_M]/1 mL; VISCUM ALBUM FRUITING TOP 1 [hp_M]/1 mL; ZINC 1 [hp_M]/1 mL
INACTIVE INGREDIENTS: ALCOHOL

DRUG FACTS:

ACTIVE INGREDIENTS:

Aqua Sulis 30C, 200C, 1M, 10M, Argentum Metallicum 1M, 10M, Aurum Metallicum 1M, 10M, Cuprum Metallicum 1M, 10M, Lapis Albus 1M, 10M, Manganum Metallicum 1M, 10M, Vanadium Metallicum 1M, 10M, Viscum Album 1M, 10M, Zincum Metallicum 1M, 10M.

PURPOSE:

Aqua Sulis – Self Induced Vertigo, Argentum Metallicum – Light Sensitivity, Aurum Metallicum – Mood Swings, Cuprum Metallicum – Poor Memory, Lapis Albus – Mood Swings, Manganum Metallicum – Light Sensitivity, Vanadium Metallicum – Self Induced Vertigo, Viscum Album – Poor Memory, Zincum Metallicum – Light Sensitivity

USES:

• For the temporary relief from symptoms including:

• self induced vertigo • light sensitivity • mood swings • poor memory

These statements are based upon homeopathic principles. They have not been reviewed by the Food and Drug Administration.

WARNINGS:

If pregnant or breast-feeding, ask a health professional before use.

Keep out of reach of children. In case of overdose, contact a physician or Poison Control Center right away.

Tamper Evident: Sealed for your protection. Do not use if seal is broken or missing.

KEEP OUT OF REACH OF CHILDREN:

In case of overdose, contact a physician or Poison Control Center right away.

DIRECTIONS:

1-10 drops under the tongue, 3 times a day or as directed by a health professional. Consult a physician for use in children under 12 years of age.

INACTIVE INGREDIENTS:

Demineralized water, 25% ethanol

QUESTIONS:

Dist. By: Deseret Biologicals, Inc.
469 W. Parkland Drive
Sandy, UT 84070

www.desbio.com

800-827-8204

PACKAGE LABEL DISPLAY:

DesBio

PEMF Optimizer

Homeopathic

NDC 43742-0693-1

1 FL OZ (30 ml)